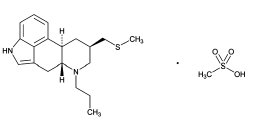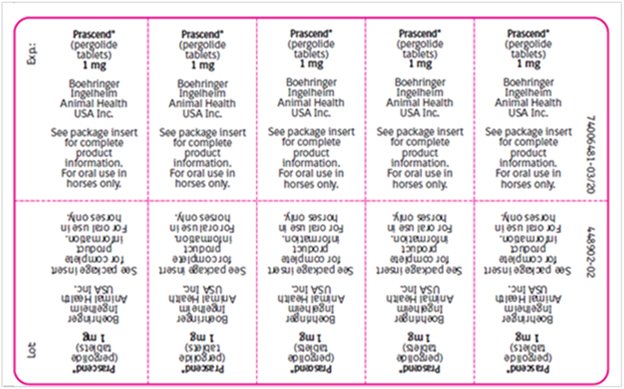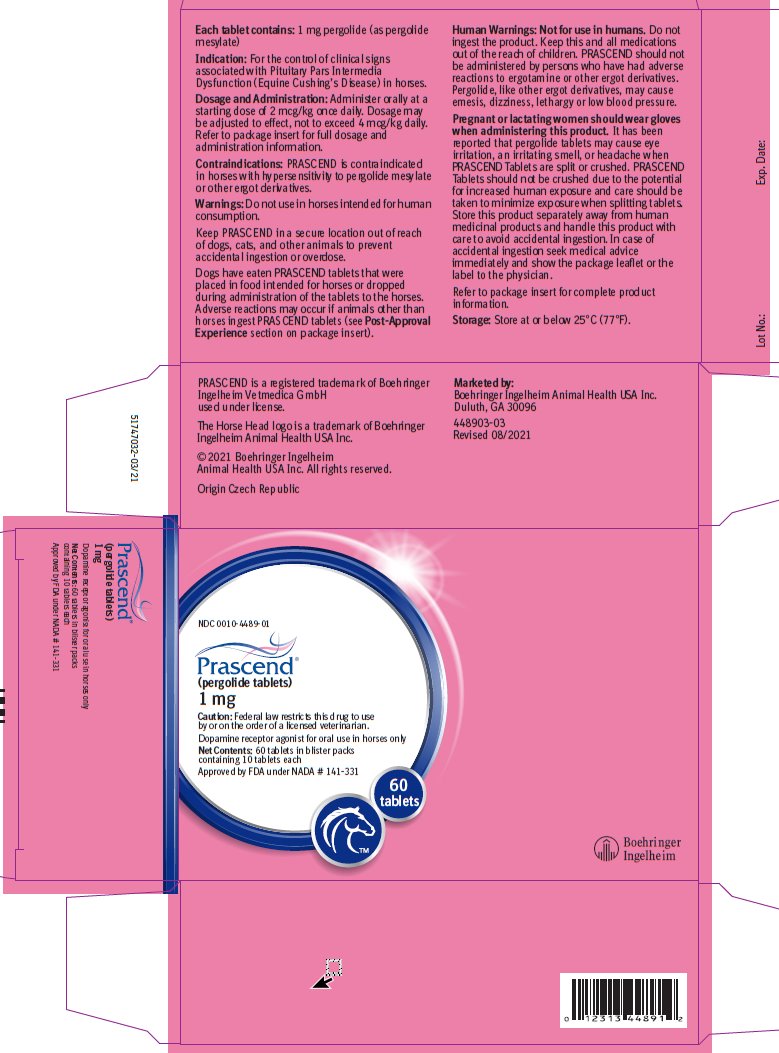 DRUG LABEL: Prascend
NDC: 0010-4489 | Form: TABLET
Manufacturer: Boehringer Ingelheim Animal Health USA Inc.
Category: animal | Type: PRESCRIPTION ANIMAL DRUG LABEL
Date: 20251223

ACTIVE INGREDIENTS: PERGOLIDE MESYLATE 1 mg/1 1

Prascend®
(pergolide tablets)
1 mg

Dopamine receptor agonist for oral use in horses only

Caution:

Federal law restricts this drug to use by or on the order of a licensed veterinarian.

Description:

PRASCEND Tablets are rectangular light red colored, half-scored tablets containing 1 mg pergolide, as pergolide mesylate. Pergolide mesylate is a synthetic ergot derivative and is a potent dopamine receptor agonist. The chemical name of pergolide mesylate is 8β-[(Methylthio) methyl]-6-propylergoline monomethanesulfonate.

The chemical structure is:

Indication:

For the control of clinical signs associated with Pituitary Pars Intermedia Dysfunction (Equine Cushing’s Disease) in horses.

Dosage and Administration:

Administer orally at a starting dose of 2 mcg/kg once daily. Dosage may be adjusted to effect, not to exceed 4 mcg/kg daily.

It has been reported that pergolide tablets may cause eye irritation, an irritating smell, or headache when PRASCEND Tablets are split or crushed. PRASCEND Tablets should not be crushed due to the potential for increased human exposure and care should be taken to minimize exposure when splitting tablets.

The tablets are scored and the calculated dosage should be provided to the nearest one-half tablet increment (see Table 1).

Table 1 Dosing Table

 | Dosage
Body weight | 2 mcg/kg | 4 mcg/kg
136 - 340 kg; (300 - 749 lb) | 0.5 tablet | 1 tablet
341 - 567 kg; (750 - 1,249 lb) | 1 tablet | 2 tablets
568 - 795 kg; (1,250 - 1,749 lb) | 1.5 tablets | 3 tablets
796 - 1,022 kg; (1,750 - 2,249 lb) | 2 tablets | 4 tablets

Dosing should be titrated according to individual response to therapy to achieve the lowest effective dose. Dose titration is based on improvement in clinical signs associated with Pituitary Pars Intermedia Dysfunction (PPID) and/or improvement or normalization of endocrine tests (for example, dexamethasone suppression test or endogenous ACTH test).

In some cases, adverse events were reported after a dose increase (see Post-Approval Experience).

If signs of dose intolerance develop, the dose should be decreased by half for 3 to 5 days and then titrated back up in 2 mcg/kg increments every 2 weeks until the desired effect is achieved.

Contraindications:

PRASCEND is contraindicated in horses with hypersensitivity to pergolide mesylate or other ergot derivatives.

Warnings:

Do not use in horses intended for human consumption.

Keep PRASCEND in a secure location out of reach of dogs, cats, and other animals to prevent accidental ingestion or overdose.

Dogs have eaten PRASCEND tablets that were placed in food intended for horses or dropped during administration of the tablets to the horses. Adverse reactions may occur if animals other than horses ingest PRASCEND tablets (see Post-Approval Experience).

Human Warnings:

Not for use in humans. Do not ingest the product. Keep this and all medications out of the reach of children. PRASCEND should not be administered by persons who have had adverse reactions to ergotamine or other ergot derivatives.

Pergolide, like other ergot derivatives, may cause emesis, dizziness, lethargy or low blood pressure.

Pregnant or lactating women should wear gloves when administering this product. It has been reported that pergolide tablets may cause eye irritation, an irritating smell, or headache when PRASCEND Tablets are split or crushed. PRASCEND Tablets should not be crushed due to the potential for increased human exposure and care should be taken to minimize exposure when splitting tablets. Store this product separately away from human medicinal products and handle this product with care to avoid accidental ingestion.

In case of accidental ingestion seek medical advice immediately and show the package leaflet or the label to the physician.

Precautions:

Treatment with PRASCEND may cause inappetence.

The use of PRASCEND in breeding, pregnant, or lactating horses has not been evaluated. The effects of pergolide mesylate on breeding, pregnant, or lactating horses are not known; however, the pharmacologic action of pergolide mesylate suggests that it may interfere with reproductive functions such as lactation. PRASCEND is approximately 90% associated with plasma proteins. Use caution if administering PRASCEND with other drugs that affect protein binding. Dopamine antagonists, such as neuroleptics (phenothiazines, domperidone) or metoclopramide, ordinarily should not be administered concurrently with PRASCEND (a dopamine agonist) since these agents may diminish the effectiveness of PRASCEND.

Adverse Reactions:

Pre-Approval Experience:

A total of 122 horses treated with PRASCEND Tablets for six months were included in a field study safety analysis.

Table 2 Summary of the most common adverse reactions (N=122)
Clinical sign | # Cases | Cases (%)
Decreased appetite | 40 | 32.8
Lameness | 22 | 18.0
Diarrhea/Loose stool | 12 | 9.8
Colic | 12 | 9.8
Lethargy | 12 | 9.8
Abnormal Weight Loss | 11 | 9.0
Laminitis* | 10 | 8.2
Heart murmur | 10 | 8.2
Death | 8 | 6.6
Tooth disorder | 8 | 6.6
Skin abscess | 7 | 5.7
Musculoskeletal pain | 6 | 4.9
Behavior change | 6 | 4.9

*Three new cases and 7 pre-existing, recurring cases

Inappetence or decreased appetite occurred at one or more meals in 40 of 122 horses treated with PRASCEND. At the baseline evaluation 1.6% of owners reported a history of inappetence or decreased appetite as compared to the 32.8% of horses that experienced inappetence or decreased appetite during the study. Most cases of inappetence were transient and occurred during the first month of treatment; however, some horses experienced sporadic inappetence throughout the study. Two horses required a temporary reduction in dose due to inappetence during the first month of the study. Both horses returned to their original dose within 30 days.

Weight loss occurred in more than half of the horses in this study; however, weight loss that was considered abnormal was only reported in 11 horses.

Lethargy was reported in 9.8% of horses during the study, and was not reported in any horses at the baseline evaluation.

Behavioral changes were noted in 6 horses including aggression, kicking, agitation, nervous behavior and increased activity. One horse required a temporary reduction in dose due to energetic behavior during the first month of the study.

Eight horses died or were euthanized during the study due to worsening of pre-existing conditions (laminitis, dental disease, septic tenosynovitis) or colic (strangulating lipomas, large colon volvulus).

One mare was inadvertently enrolled in the study while pregnant and experienced dystocia resulting in the death of the foal.

Post-Approval Experience (2019):

The following adverse events are based on post approval adverse drug experience reporting for PRASCEND. Not all adverse events are reported. It is not always possible to reliably estimate the adverse event frequency or establish a causal relationship to product exposure using these data.

The following adverse events in horses are categorized in order of decreasing reporting frequency by body system and in decreasing order of reporting frequency within each body system:

General: anorexia, lethargy, weight loss

Gastrointestinal: diarrhea, abdominal pain/colic

Dermatological: alopecia, hyperhidrosis, dermatitis

Musculoskeletal: laminitis, muscle stiffness/soreness

Neurological: ataxia, seizure, muscle tremors

Behavioral: aggression (to other horses and humans), hyperactivity (anxiety, agitation), other behavioral changes (stud-like behavior, spooky, unpredictable, confused)

Clinical pathology: anemia, elevated liver enzymes, thrombocytopenia

The above adverse events were reported in some horses at starting dose levels, while in the others following a dose increase.

Death (including euthanasia) has been reported.

Adverse events have been reported in dogs following ingestion of tablets prepared for administration to horses.

To report suspected adverse reactions, to obtain a Safety Data Sheet (SDS), or for technical assistance, contact Boehringer Ingelheim Animal Health USA Inc. at 1-888-637-4251. For additional information about adverse drug experience reporting for animal drugs, contact the FDA at 1-888-FDA-VETS or online at http://www.fda.gov/reportanimalae.

Clinical Pharmacology:

Pergolide mesylate is a synthetic ergot derivative and is a potent dopamine receptor agonist. As with other dopamine agonists, pergolide inhibits the release of prolactin which suggests that it may interfere with lactation. In horses with PPID, pergolide is believed to exert its therapeutic effect by stimulating dopamine receptors, and has been shown to decrease the plasma levels of adrenocorticotropic hormone (ACTH), melanocyte stimulating hormone (MSH), and other pro-opiomelanocortin peptides. ^1

Pharmacokinetic information in the horse is based on a study using single oral doses of 10 mcg/kg in six healthy mares between 3 and 17 years of age. ^2 Pergolide was rapidly absorbed; the mean maximum concentration (Cmax) was 4.05±2.02 ng/mL with the median time to maximum concentration (Tmax) being 0.415 hours.

The area under the curve (AUC) was 14.08±7.46 hr∙ng/mL. The mean half life (T1/2) was 5.86±3.42 hours; the mean apparent oral clearance (CL/F) was 1204 mL/kg/hr; and the mean apparent volume of distribution (V/F) was 3082±1354 mL/kg.

Effectiveness:

An open-label, historical control, field study evaluated the effectiveness of PRASCEND for the control of clinical signs of PPID. A total of 122 horses with PPID were enrolled in the study, 113 of which were included in effectiveness evaluations. The success of each horse was based on results of endocrinology testing (dexamethasone suppression test or endogenous ACTH test) and/or improvement in clinical signs related to PPID (hirsutism, hyperhidrosis, polyuria/polydypsia, abnormal fat distribution, and/or muscle-wasting) on the Day 180 evaluation. Based on endocrine testing and investigators’ clinical assessment scores, 86 (76.1%) of the 113 evaluable cases were treatment successes.

Table 3 Proportion of Treatment Successes on Day 180

Percent success | Lower bound: one-sided 95% confidence interval
76.1% (86/113) | 68.6%

Enrolled horses were diagnosed with PPID based on the presence of hirsutism and an abnormal pre-study endocrine test result. All horses were treated with 2 mcg/kg PRASCEND (to the nearest one-half tablet) orally once daily for the first three months. If the endocrine test result on Day 90 was normal or adequately improved, the horse continued on the same dose through Day 180. If the endocrine test result on Day 90 was abnormal, the dose increased to 4 mcg/kg given once daily through Day 180. Forty-seven (41.6%) of the 113 horses included in the effectiveness database required a dose increase at Day 90.

Improvement was noted in scores for all clinical sign categories and in mean results for endocrine tests.

Table 4 Percent of Animals with Improvement in Clinical Signs Relative to Baseline Scores
Clinical sign | Day 90±7 (%) | Day 180±7 (%)
Hirsutism | 32.7% | 89.2%
Hyperhidrosis | 27.4% | 42.3%
Polyuria / polydypsia | 31.0% | 34.2%
Abnormal fat distribution | 21.2% | 33.3%
Muscle wasting | 36.3% | 46.0%

Table 5 Endocrine test results (mean values)
Test | # Animals | Baseline | Day 90 | Day 180
ACTH; (pg/mL) | 20 | 73.53 | 51.12 | 45.08
DST**; (mcg/dL) | 93 | 3.12 | 1.39 | 1.47

** Dexamethasone suppression test: Post dexamethasone cortisol concentration

Animal Safety:

In a six month target animal safety study healthy adult horses received PRASCEND administered orally, once daily, at doses of either 0 mcg/kg, 4 mcg/kg, 6 mcg/kg, or 8 mcg/kg (0X, 1X, 1.5X, or 2X the maximum recommended dose). There were eight healthy horses (four males and four females) in each treatment group. Doses were prepared by dissolving tablets in approximately 10 mL of a 50% sugar water solution.

PRASCEND treated groups had lower mean heart rates and higher mean temperatures than the control group. Horses in all treatment groups had minimum heart rates within the normal range and maximum temperatures below 101.5°F. One 1.5X horse experienced a mild episode of spasmodic colic on Day 3 that resolved after treatment with flunixin meglumine.

Mean red blood cell counts and hemoglobin values were lower in PRASCEND treated groups as compared to the control group. Other hematology parameters including hematocrit, white blood cells, absolute neutrophils, and absolute lymphocytes exhibited mild, transient decreases as compared to the control group. The hematology parameters generally decreased over the first 30 to 60 days after treatment initiation and then returned to values similar to pre-treatment levels. No treatment related alterations were identified on histopathology evaluation of bone marrow.

Storage:

Store at or below 25°C (77°F).

How Supplied:

PRASCEND Tablets are available in 1 mg strength – packaged 10 tablets per blister and 60 or 160 tablets per carton.

NDC 0010-4489-01 – 60 tablets

NDC 0010-4489-02 – 160 tablets

Approved by FDA under NADA # 141-331

References:

^1 Orth, D.N., Holscher, M.A., Wilson, M.G., et al. (1982) Equine Cushing’s Disease: Plasma Immunoreactive Proopiolipomelanocortin Peptide and Cortisol Levels Basally and in Response to Diagnostic Tests. Endocrinology. 110(4):1430-41

^2 Wright A, Gehring R, Coetzee H (2008.) Pharmacokinetics of pergolide in normal mares. American College of Veterinary Internal Medicine Forum, Abstract #36, San Antonio, TX.

Marketed by:
Boehringer Ingelheim Animal Health USA Inc.
Duluth, GA 30096

Origin Czech Republic

PRASCEND is a registered trademark of Boehringer Ingelheim Vetmedica GmbH used under license.

© 2021 Boehringer Ingelheim Animal Health USA Inc. All rights reserved.

448901-03

Revised 05/2021

Principal Display Panel - 60 – Tablet Display Carton

NDC 0010-4489-01

Prascend®

(pergolide tablets)

1 mg

Caution: Federal law restricts this drug to use by or on the order of a licensed veterinarian.

Dopamine receptor agonist for oral use in horses only

Net Contents: 60 tablets in blister packs containing 10 tablets each

Approved by FDA under NADA # 141-331